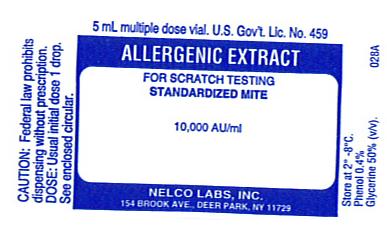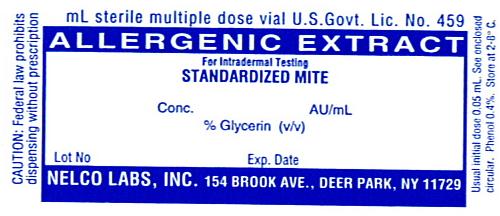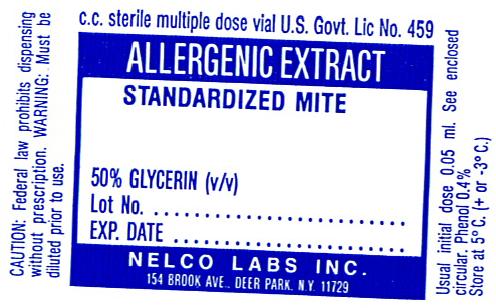 DRUG LABEL: Standardized Mite Dermatophagoides farinae
NDC: 36987-1844 | Form: INJECTION, SOLUTION
Manufacturer: Nelco Laboratories, Inc.
Category: prescription | Type: HUMAN PRESCRIPTION DRUG LABEL
Date: 20091201

ACTIVE INGREDIENTS: DERMATOPHAGOIDES FARINAE 10000 [AU]/1 mL
INACTIVE INGREDIENTS: SODIUM CHLORIDE; SODIUM PHOSPHATE, DIBASIC; POTASSIUM PHOSPHATE, MONOBASIC; WATER; PHENOL; GLYCERIN

Allergenic Extract

WARNINGS

Standardized Allergenic Extract is intended for use by physicians who are experienced in the administration of standardized (AU/mL) allergenic extracts for immunotherapy and the emergency care of anaphylaxis, or for use under the guidance of an allergy specialist. Standardized allergenic extracts are not directly interchangeable with other allergenic extracts. The initial dose must be based on skin testing as described in the DOSAGE AND ADMINISTRATION section of this insert. Patients being switched from other types of extract to standardized allergenic extracts should be started as though they were coming under treatment for the first time. Standardized Mite extract is NOT directly interchangeable with non-standardized Mite extract.

This product should not be injected intravenously. Deep subcutaneous routes have proven to be safe. Sensitive patients may experience severe anaphylactic reactions resulting in respiratory obstruction, shock, coma and/or death.(14) Patients should be observed for at least 30 minutes following treatment and emergency measures and personnel trained in their use should be immediately available in the event of a life threatening reaction. (See Precautions)

Allergenic extracts may be used with caution for patients with unstable or steroid-dependent asthma or with underlying cardiovascular disease. (Contraindications)

Extreme caution should be taken when using allergenic extracts for patients who are taking beta-blocker medications. In the event of a serious adverse reaction associated with the use of allergenic extracts, patients receiving beta-blockers may not be responsive to epinephrine or inhaled bronchodialators.

Serious adverse reactions should be reported to Nelco Laboratories immediately and a report filed to: MedWatch, The FDA Medical Product Problem Reporting Program, at 5600 Fishers Lane, Rockville, Md. 20852-9787, call 1-800-FDA-1088.

DESCRIPTION

Standardized mite extract is a sterile injectable solution containing the extractable of Dermatophagoides farinae or Dermatophagoides pteronyssinus, 0.5% NaCl, 0.08% Na2HPO4, 0.036% KH2PO4, distilled water for injection, 0.4%, phenol as preservative and 50% glycerin by volume in sterile containers. All extracts are aseptically filled. Standardized mite extract is to be administered by prick-puncture or intradermal routes when used for diagnostic purposes and administered subcutaneously when used for immunotherapy injections.

It has been recognized that mites are one of the most common allergens in House Dust (1,2). Recent research and extensive clinical trials have shown that the mite component is important enough to separate it from the other antigenic components of House Dust. The two species of Dermatophagoides are found in the United States.(4)

Persons thought to be allergic to House Dust should be tested for sensitivity to mites. Standardized extracts have been prepared to diagnose and treat with D. farinae and D. pteronyssinus.

The Allergy Units are assigned to these extracts based on the relative potency by ELISA Inhibition to the Center for Biologics Evaluation and Research (CBER) reference. The CBER mite reference preparation has been assigned 10,000 AU/mL, based on quantitative skin assays.(11)

Extracts are prepared from supplied raw material containing greater than 99% pure adult mites and mite stages by actual count. The mites have been grown on a medium containing yeast and pork products. Cleaning of the raw material removes at least 99% of the medium. This medium contains no material of human origin. The extracting fluid contains 0.5% NaCl, 0.08% Na2HPO4, 0.036% KH2PO4, distilled water for injection, 0.4% phenol as preservative and 50% glycerin by volume as stabilizer.

The raw material is extracted with diluent, glycerinated, and the potency on the label is expressed in Allergy Units (AU/mL). Several manufacturers submitted intradermal skin test data on Biopol Laboratories mite medium extract using patients who were puncture test positive (Σ E ≥ 40 mm) to either D. farinae or D. pteronyssinus extracts. By intradermal testing, there was 1 positive (Σ E ≥ 20 mm) in 44 individuals at an estimated 1% level of medium contamination of mites and 4 positives in 40 individuals at an estimated 10% contamination.(5) Two of the individuals who were skin test positive to mite extract and who were also skin test positive to mite medium extract were also skin tested by the puncture method with an extract of yeast (Sacchoromyces spp) and were positive.

CLINICAL PHARMACOLOGY

The mode of action of allergenic extracts is still under investigation. The pharmacological action of allergenic extracts used diagnostically is based on the liberation of histamine and other substances when the allergen reacts with IgE antibodies attached to the mast cells. When allergen extracts are used for therapeutic immunotherapy, the effect is an increase in immunoglobulin G (IgG) and an increased T suppresser lymphocyte which interferes with the allergenic response.(15) Although immunotherapy may be considered as immunosuppression, in which the production of allergen-specific antibody is inhibited, the mechanism of the clinical effectiveness of immunotherapy remains under investigation.

INDICATIONS AND USAGE

Standardized mite allergenic extracts are intended for use in the diagnosis and therapy of D.farinae and D.pteronyssinus mite allergy, as established by allergy history and skin test reactivity (6,10). Standardized Mite extracts are not interchangeable with non standardized mite extracts. To select patients for a confirmation of allergic disease diagnosis and/or treatment with allergen extracts, screening tests should be done using in vivo identification testing methods (i.e. scratch or intradermal testing).(13)

Standardized mite extract containing equal parts of D.farinae and D.pteronyssinus is intended for therapy only. The use of standardized mites extract is indicated for hypersensitization treatment and may be used as part of the over-all management of the allergic patient. This treatment is particularly to be recommended when a patient's sensitivity to mite has been determined initially by scratch or intradermal skin tests.

CONTRAINDICATIONS

This product should not be used if the patient has asthma, cardiovascular disease, emphysema, diabetes, bleeding diathesis or pregnancy, unless a specific diagnosis of type 1 allergy to mite is made based on skin testing and the benefits of treatment outweigh the risks of an adverse reaction during testing or treatment. Mite extracts are not indicated for use in patients who are not clinically allergic to mite or who are not skin reactive to mite. Limitations on treatment using mite extract should be considered when treating very young patients, geriatric patients or patients suffering from auto-immune disorders or severe and unstable allergic conditions.

WARNINGS

Standardized Mites extract labeled in AU/mL are not interchangeable with non-standardized mite extracts.

Concentrated extracts must be diluted with sterile diluent prior to first use on a patient for treatment or intradermal testing.

DO NOT INJECT INTRAVENOUSLY. All concentrates of allergenic extracts have the ability to cause serious local and systemic reactions including death in sensitive patients. Sensitive patients may experience severe anaphylactic reactions resulting in respiratory obstruction, shock, coma and /or death. Allergenic extract should be temporarily withheld from patients or the dose of the extract adjusted downward if any of the following conditions exist: (1) Severe symptoms of rhinitis and/or asthma, (2) Infections or flu accompanied by fever and (3) Exposure to excessive amounts of clinically relevant allergen prior to a scheduled injection.

PRECAUTIONS

General Information:

Epinephrine 1:1000 should be available as well as personnel trained in administering emergency treatment. Allergenic Extracts are not intended for intravenous injections. For safe and effective use of allergen extracts, sterile diluent, sterile vials, sterile syringes should be used and aseptic precautions observed when making a dilution and/or administering the allergen extract injection. A sterile tuberculin syringe graduated in 0.1 mL units to measure each dose for the prescribed dilution should be used. Parenteral drug products should be inspected visually for particulate matter and discoloration prior to administration, whenever solution and container permit.

To reduce the risk of an occurrence of adverse reactions, begin with a careful personal history plus a physical exam. Confirm your findings with scratch or intradermal skin testing. Patients should be observed for 30 minutes after any test.

Information for Patients: All concentrates of allergen extracts including standardized pollen extracts, have the potential to cause serious local and systemic reactions including death, in sensitive patients. To minimize this potential hazard, the relative sensitivity of the patient must be assessed from an allergic history and from clinical observations. In certain individuals, life-threatening reactions may occur. Patients should be informed of this risk prior to skin testing and immunotherapy. Patients should be instructed to recognize adverse reaction symptoms that may occur and to report all adverse reactions to a physician. Patients should be told to wait in the office after injections for at least 30 minutes.

Drug Interaction: Antihistamines and Hydroxyzine can significantly inhibit the immediate skin test reactions as they tend to neutralize or antagonize the action of histamine (14). This effect has been primarily documented when testing was performed within 1 to 2 hours after drug ingestion. Although partial inhibition of the skin test reaction had been observed for longer periods, it was minor. Epinephrine injection inhibits the immediate skin test reactions for several hours. Patients on delayed absorption antihistamine tablets should be free of such medication for 48 hours before testing. Patients using Astemizole (Hismanal) may experience prolonged suppression and should be free from such medication for up to 6 to 8 weeks prior to testing. Refer to package insert from applicable long acting antihistamine manufacturers for additional information. In the event of a serious adverse reaction, patients receiving beta-blockers may not be responsive to epinephrine or inhaled bronchodilators.

Carcinogenesis, mutagenesis, impairment of fertility.

Long term studies in animals have not been conducted with allergenic extracts, especially mite extracts, to determine their potential carcinogenicity, mutagenicity or impairment of fertility.

Pregnancy: Category C. Animal reproduction studies have not been conducted with D. farinae or D. pteronyssinus mite extracts, it is not known whether this extract can incur fetal harm when administered to a pregnant women or can effect reproduction capacity. Standardized D.farinae or D.pteronyssinus Mite extract should be given to pregnant women and nursing mothers only if clearly needed.

Nursing Mothers: It is not known whether this drug is excreted in human milk. Because many drugs are excreted in human milk, caution should be exercised when Allergenic Extract, Standardized Mites, is administered to a nursing woman. There are no current studies on secretion of the extract components in human milk, or their effect on the nursing infant.

Pediatric Use: Children have been used extensively as patients in studies with mite extracts. However, it is recommended that children be treated only when indicated (6,7,8). Allergenic extracts have been tested in children over two years of age (9). (See WARNINGS and ADVERSE REACTIONS).

ADVERSE REACTIONS

Anaphylaxis and other systemic reactions may occur such as induced asthma, itching of nose and throat, breathlessness, urticaria and local reactions. Local reactions can be defined as an area of large erythema, swelling or pruritus at the injection site. Further indications of adverse reactions are edema, wheezing, dyspnea, locomotive impairment, marked perspiration, coughing, hypertension, shock and upper airway obstruction.

Adverse systemic reactions usually occur within minutes and consist primarily of allergic symptoms such as generalized skin erythema, urticaria, pruritus, angioedema, rhinitis, wheezing, laryngeal edema and hypotension. Less commonly, nausea, emesis, abdominal cramps, diarrhea and uterine contractions may occur. Severe reactions may cause shock and loss of consciousness. Fatalities have occurred rarely. These systemic reactions occur with varying frequency in different clinics. To some extent, the reaction rate is related to the type and dose of administered extract and to the degree of sensitivity of the patient. Despite all precautions, occasional reactions are unavoidable.

Reports from regulatory authorities in Sweden to the Center for Biologics Evaluation and Research (CBER) indicated that several deaths have been associated with the use of mite extracts. The CBER was subsequently informed that these deaths may have been related to use by physicians or other health professionals untrained in the administration of potent allergens rather than a product defect. It should be noted that anaphylaxis and deaths following the injection of mite extracts have also been reported by the British Committee on Safety in Medicine in the British Medical Journal, V293,pp948,1986.

Local reactions consisting of erythema, itching, swelling tenderness and sometimes pain may occur at the injection site. These reactions may appear within a few minutes to hours and persist for several days. Local cold applications and oral antihistamines may be effective treatment. For marked and prolonged local reactions steroids may be helpful.

OVERDOSAGE

Overdose can cause both local and systemic reactions. Overdose is prevented by careful observation and questioning of the patient about the previous injection.

The treatment of systemic allergic reactions is dependent upon the symptom complex. In cases of an occurrence of a systemic or anaphylactic reaction, apply a tourniquet above the site of injection and inject intramuscularly or subcutaneously 0.3 to 0.5mL of 1:1000 Epinephrine Hydrochloride into the opposite arm. The dose may be repeated in 5-10 minutes if necessary. Loosen the tourniquet at least every 10 minutes. The Epinephrine Hydrochloride 1:1000 dose for infants to 2 years is 0.05 to 0.1 mL: for children 2 to 6 years it is 0.15 mL:, for children 6-12 years it is 0.2 mL.

Patients unresponsive to Epinephrine may be treated with Theophylline. Studies on asthmatic subjects reveal that plasma concentrations of Theophylline of 5 to 20 µg/mL are associated with therapeutic effects. Toxicity is particularly apparent at concentrations greater than 20 µg/mL. A loading dose of Aminophylline of 5.8 mg/kg intravenously followed by 0.9 mg/kg per hour results in plasma concentrations of approximately 10 µg/mL. (Mitenko and Ogilive, Nicholoson and Chick,1973)

Other beta-adrenergic drugs such as Isoproterenol, Isoetharine, or Albuterol may be used by inhalation. The usual dose to relieve broncho-constriction in asthma is 0.5 mL or the 0.5% solution for Isoproterenol HCl. The Albuterol inhaler delivers approximately 90 mcg of Albuterol from the mouthpiece. The usual dosage for adults and children would be two inhalations repeated every 4-6 hours. Isoetharine supplied in the Bronkometer unit delivers approximately 340 mcg Isoetharine. The average dose is one to two inhalations.

Respiratory obstruction not responding to parenteral or inhaled bronchodilators may require Theophylline, oxygen, intubation and the use of life support systems. Parenteral fluid and/or plasma expanders may be utilized for treatment of shock. Adrenocorticosteroids may be administered parenterally or intravenously.

Antihistamines may offer relief of recurrent urticaria, associated skin reactions and gastrointestinal symptoms. Persistent wheezing may necessitate intravenous aminophylline treatment. For profound shock and hypotension, intravenous fluids, vasopressor and oxygen may also be needed. Maintenance of a patent airway is critical if upper and lower airway obstruction is present. Corticosteroids may provide benefit if symptoms are prolonged or recurrent.

DOSAGE AND ADMINISTRATION

It is imperative that the physician determine the initial dose of the product by skin testing. Patients being switched from a Standardized Mite extract to a new Standardized Mite extract (both labeled in AU/mL) should be skin tested with both extracts to determine the relative potency of the extracts and the dosage adjusted accordingly.

For safe and effective use of allergen extracts, sterile solutions, vials, syringes, etc. should be used and aseptic precautions observed in making dilution's. The usual precautions to be observed in administering extracts are necessary. A sterile tuberculin syringe graduated in 0.1 mL units to measure each dose for the prescribed dilution should be used.

Recommended dosage and range:(Diagnostic) The concentration of Standardized Mite extract for Scratch or Prick-puncture testing is 10,000 AU/mL, glycerinated, supplied in 5 mL dropper vials. Skin tests are graded in terms of the wheal and erythema response noted at 10 to 20 minutes. Wheal and erythema size may be recorded by actual measurement or the extent of both responses.

Prick-puncture tests on Mite allergic subjects: 10 puncture tests (bifurcated needle) on mite allergic subjects yielded the following:

 | # Person | Mean sum of wheal | Range | Mean sum of Erythema | Range (mm)
D. farinae | 10 | 17.4 mm | 12-21 mm | 78.8 mm | 63-97 mm
D. pteronyssinus | 10 | 18.0 mm | 10-37 mm | 68.7 mm | 46-114 mm

Intradermal tests (using 0.05 mL) on 10 puncture positive patients AU/mL to elicit 50 mm sum of dia. of erythema reaction (10)

 | # Persons | Mean | Range (AU/mL)
D. farinae | 10 | 0.029 AU/mL | 0.077-0.005 AU/mL
D. pteronyssinus | 10 | 0.024 AU/mL | 0.78-0.0004 AU/mL

Patients with a negative scratch or prick-puncture test: Patients who do not react to a valid scratch or prick- puncture test should be tested intradermally with a 0.02 to 0.05 mL of a 50 AU/mL extract solution. If this test is negative, a second intradermal test may be performed using a 100 AU/mL extract dilution. The negative puncture test control must be diluted appropriately for ID use. It is supplied in 5 mL and 10 mL vials of 50% glycerin (v/v).

To prepare a 50 AU/mL dilution from 10,000 AU/mL vial:

Take 5.0mL of 10,000AU/mL + 5.0 mL of diluent = Vial A @5,000 AU/mL.

Take 1.0 of Vial A + 9.0 mL diluent = Vial B @ 500 AU/mL.

Take 1.0 of Vial B + 9.0 mL diluent = Vial C @ 50 AU/mL.

Patients tested only by the intradermal method: Patients being suspected of being highly allergic should be tested with 0.02 to 0.05 mL of a 0.1 AU/mL dilution.(3) A negative test should be followed by repeat tests using progressively stronger concentrations until the maximal recommended strength of 100 AU/mL is reached. The negative puncture test control must be diluted appropriately for intradermal use. It is supplied in 5 mL and 10 mL vials of 50% glycerin (v/v).

Recommended dosage and range: (Therapeutic) Dosage of allergenic extracts is a highly individualized matter and varies according to the degree of sensitivity of the patient, his clinical response and tolerance to the extract administered during the early phases of an injection regimen. In patients who appear to be highly sensitive by history and skin test, the initial dose of the extract should be 0.1 mL of 0.01 to 0.1 AU/mL. Patients with lesser sensitivity may be started at 1.0 to 10.0 AU/mL. The amount of allergenic extract is increased at each injection by not more than 50%-100% of the previous amount, and the next increment is governed by the response to the last injection. Large local reactions which persist longer than 24 hours are generally considered an indication for repeating the previous dose or reducing the dose. Any evidence of systemic reaction is an indication for a significant reduction (at least 50%) for the subsequent dose. Maximum dosage has not been established however, the upper limits of l mL of 10,000 AU/mL may be painful due to glycerin content. The dosage of allergenic extract does not vary significantly with the allergic disease under treatment.

After therapeutic injections patients should always be observed for at least 30 minutes. If adverse reactions appear, the next therapeutic injection of extract should be reduced to the dose which does not elicit a reaction and subsequent doses increased slowly. If local reactions occur, reduce subsequent injections to a dose which did not elicit this reaction.

Preparation Instructions: To prepare dilution for intradermal and therapeutic use, one starts with 10,000 AU/mL concentrate and makes a 1:10 dilution by adding 1.0 mL of the concentrate to 9.0 mL of sterile diluent. Subsequent dilution's are made in similar manner.

TEN-FOLD DILUTION SERIES
Dilution | Extract | Diluent mL | AU/mL
0 | Concentrate | 0 | 10,000
1 | 1 mL concentrate | 9 | 1,000
2 | 1 mL dilution #1 | 9 | 100
3 | 1 mL dilution #2 | 9 | 10
4 | 1 mL dilution #3 | 9 | 1
5 | 1 mL dilution #4 | 9 | 0.1
6 | 1 mL dilution #5 | 9 | 0.01

Intervals between doses: The optimal interval between doses of allergenic extract has not been definitely established. However, as it is customary practiced, injections are given 1,2, or 3 times per week until the maintenance dose of extract is reached. At this time, the injection interval may be increased to 2 weeks, then 3 weeks and finally to 4 weeks. If the patient does not return for 6-8 weeks after the last injection, the dose should be reduced to 25% of the last dose. If longer than 8 weeks, a dose reduction of 1,2, or 3 dilution's may be made depending on a consideration of the components and the patient's sensitivity. The dosage and the interval between injections may need to be modified according to the clinical response of the patient. When switching patients to a fresh extract the initial dose should be reduced 3/4 so that 25% of previous dose is administered.(14)

Duration of Treatment: The usual duration of treatment has not been established. A period of two or three years of injection therapy constitutes an average minimum course of treatment.

Parenteral drug products should be inspected visually for particulate matter and discoloration prior to administration, whenever solution and container permit.

HOW SUPPLIED

Diagnostic Allergens- Scratch or Prick test: 10,000 AU/mL, 50% glycerin in 5 mL dropper vials.

Intradermal test- 100 AU/mL in 5 mL or 10 mL sterile multiple dose vials.

Therapeutic allergens - In 5 mL, 10 mL, 50 mL multiple dose vials as individual allergens, stock mixture containing 5000 AU/mL of D. farinae plus 5000 AU/mL of D. pteronyssinus, or mixture prescribed by physician.

Dilution's of concentrate can be made with either buffered diluent with 0.4% phenol or 50% glycerin (v/v) with salts.

STORAGE

The expiration date of Standardized Mite extract containing 10,000 AU/mL in 50% glycerin (v/v) is listed on the container label. Store extracts upon arrival at 2° to 8°C and keep them in this range during office use.

WARRANTY: We warrant that this product was prepared and tested according to the standards of the FDA and is true to label. Because of biological differences in individuals and because allergenic extracts are manufactured to be potent and because we have no control over the conditions of use, we cannot and do not warrant either a good effect or against an ill effect following use.

REFERENCES

1. Wharton, G.W.: House Dust Mites, J.Med. Entomol.12:577,1976.

2. Vorhorst.R., M.Spieksnma and Varekamp: House Dust atopy and the house mite. Linden, Stafleu's Scientific Publishing Co.,1969.

3. Bear,H. :Allergy to House Dust Mites. Immuno Allergy Practice. 5:356, 1983.

4. Lang, J.D. and S.Mulla: Distribution and abundance of House Dust Mites.Dermatophagoides (Spp) in different zones of Southern California. Environmental Entomology 6:123, 1977.

5. Seltzer,J.M. Standardization and Relative Potency of D.farinae extract. Jour.Allergy and Clin.Immuno. Vol. 77 p204, 1986.

6. Murray,A.B. A.C. Ferguson, B.J. Morrison: Diagnosis of House Dust Mite Allergy in asthmatic children. J. Allergy Clin. Immuno. 71:21, 1983.

7. Warner,J.O., J.F.Price, J.F. Soothill, Controlled trials of hyposensitization to D.pteronyssinus in children with asthma. Lancet 2:912, 1978.

8. Smith, A.P. Hyposentization with D.pteronyssinus antigen. Trials in asthma induced by house dust. Br.Med.4.204,1971.

9. Glasser,J., Allergy in Childhood. C. Thomas, 29, 1956.

10. Pauli,G, J.C.Bessot, R.Thierry, A.Lamensons:Correlation between skin tests, inhalation tests and specific IgE in a study of 120 subjects allergic to house dust and D.pteronyssinus. Clin.Allergy 7:337,1977.

11. Quantitative Intradermal Procedure for Evaluation of Subject Sensitivity to Standardized Allergenic Extracts and for Assignment of Bioequivalent Allergy Units to Reference Preparations using the ID50EAL method. Methods & Procedures Manual, CBER, 1993.

12. Lockey,R., L.M.Benedict, P.C.Turkeltaub, S.O.Bukantz. Fatalities from immunotherapy and skin testing. J.Allergy Clin Immuno.,79(4), 1987.

13. Evans,R., H. Pence, H.Kaplan, R.Rockllin: The Effect of Immunotherapy on Humoral and Cellular Response in Ragweed Hayfever. J.Clin.Inv. 57, 1976.

14. Gleich, G., J.W. Younginger: The RAST test: A Method to Measure IgE Antiboides and the Potency of Allergy Extracts, N.Y. Acad. Sci.57 (7), 1981.

15. Ishizaka,K.: Cellular Events in the IgE Antibody Response. Adv. in Immuno. 23:50-75, 1976.

16. Bousquet.J.,Djoukadar, F.Hewitt, B.Guerin, B.Michel, Comparison of the stability of a mite and a pollen extract stored in normal conditions of use.Clin.Allergy, 15,1985.